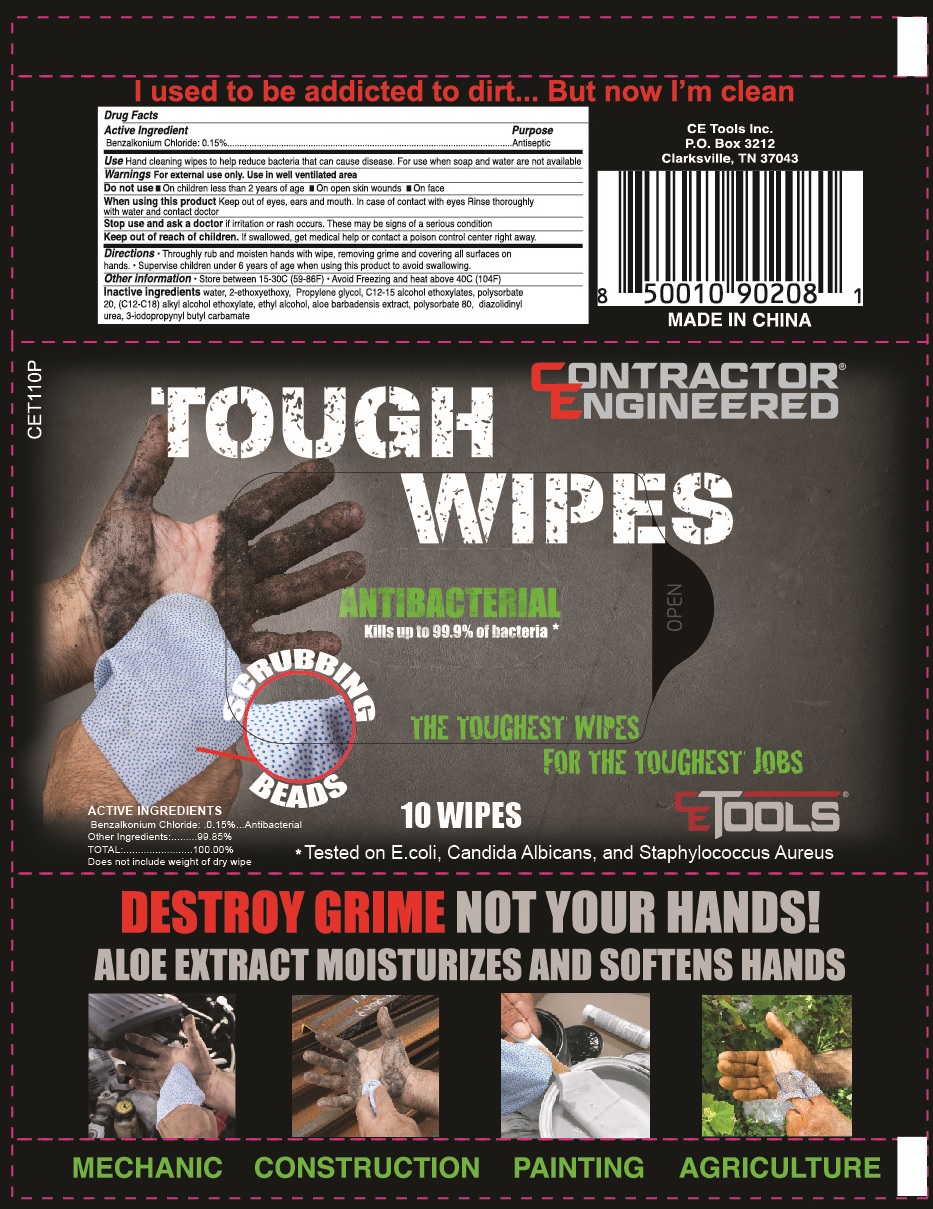 DRUG LABEL: Contractor Engineered Tough Wipes
NDC: 77435-108 | Form: SWAB
Manufacturer: HAINING LILY CLEANING PRODUCTS CO., LTD
Category: otc | Type: HUMAN OTC DRUG LABEL
Date: 20240422

ACTIVE INGREDIENTS: BENZALKONIUM CHLORIDE 0.15 g/100 g
INACTIVE INGREDIENTS: WATER; PROPYLENE GLYCOL; DIDECYLDIMONIUM CHLORIDE; DIETHYLENE GLYCOL MONOETHYL ETHER; POLYSORBATE 20

Antibacterial Wipes

Active Ingredient

Benzalkonium Chloride 0.15%

Purpose

Antiseptic

USE

- hand cleaning wipes to help reduce bacteria that can cause disease. For use when soap and water are not available

Warning

- For external use only.

When using this product keep out eyes, ears and mouth. In case of contact with eyes. Rinse thoroughly with water and contact doctor.

Stop use and ask a doctor

- if irritation or rash occurs. These may be signs of a serious condition.

Other Information：

Store between 15-30℃ (59-86℉)

Avoid freezing and heat above 40℃ (104℉)

KEEP OUT OF REACH OF CHILDREN

If swallowed,, get medical help or contact a poison control center right away.

direction

thoroughly rub and moisten hands with wipe, removing grime and covering all surfaces on hands. Supervise children under 6 years of age when using this product to avoid swallowing.

Inactive ingredients

water, 2-ethoxyethoxy, propylene glycol, c12-15 alcohol ethoxylates, polysorbate 20, (c12-18) alkyl alchol ethoxylate, ethyl alcohol, aloe barbadensis etract, polysorbate 80, diazolidinylurea, 3-iodopropynyl butyl carbamate